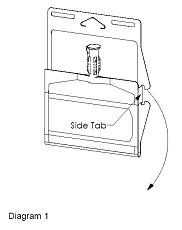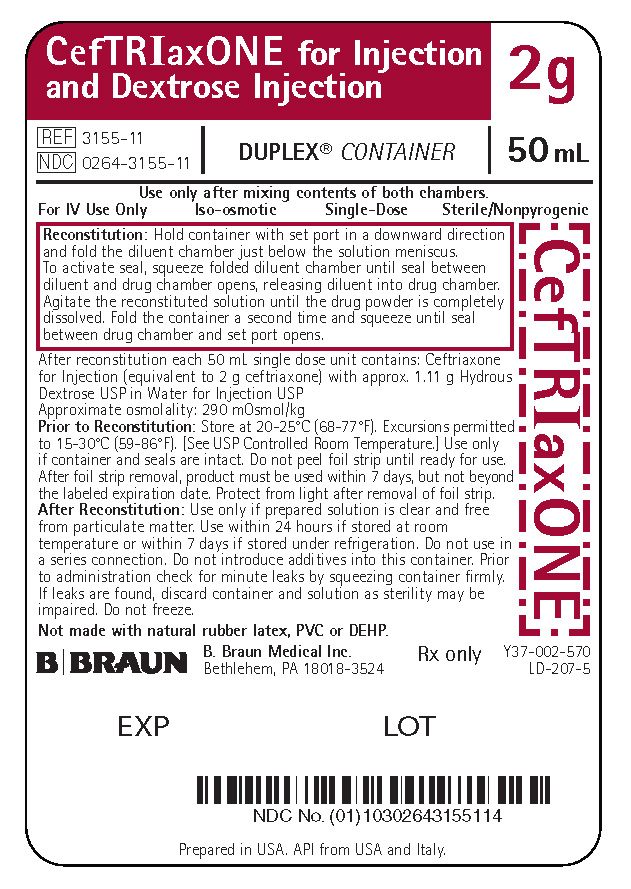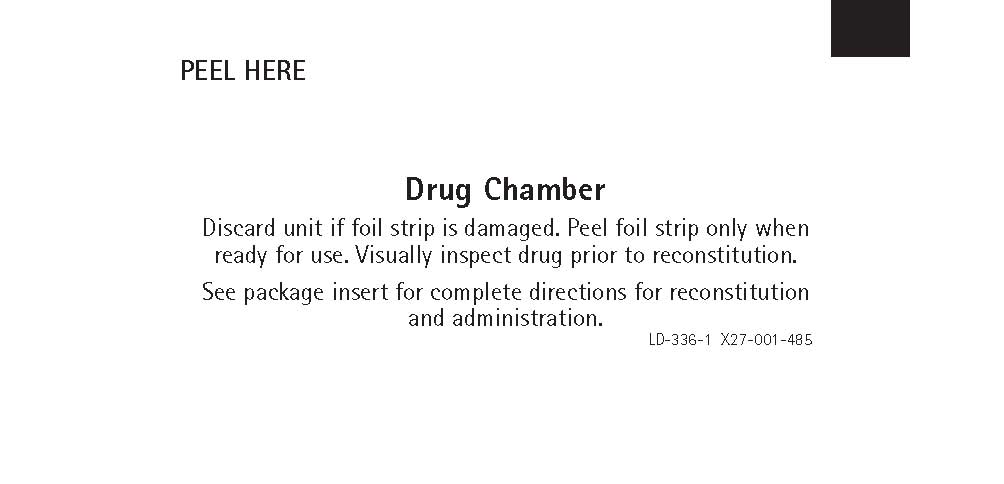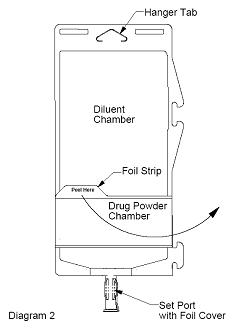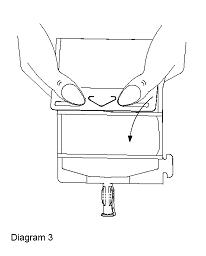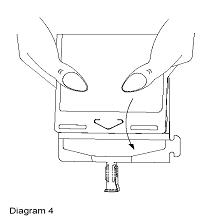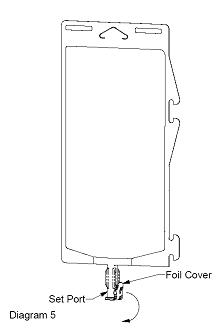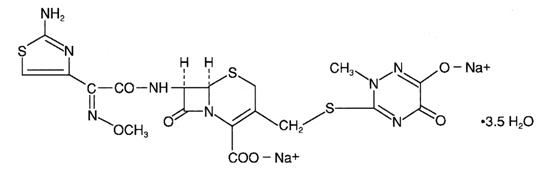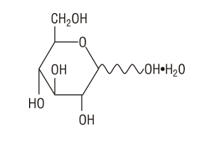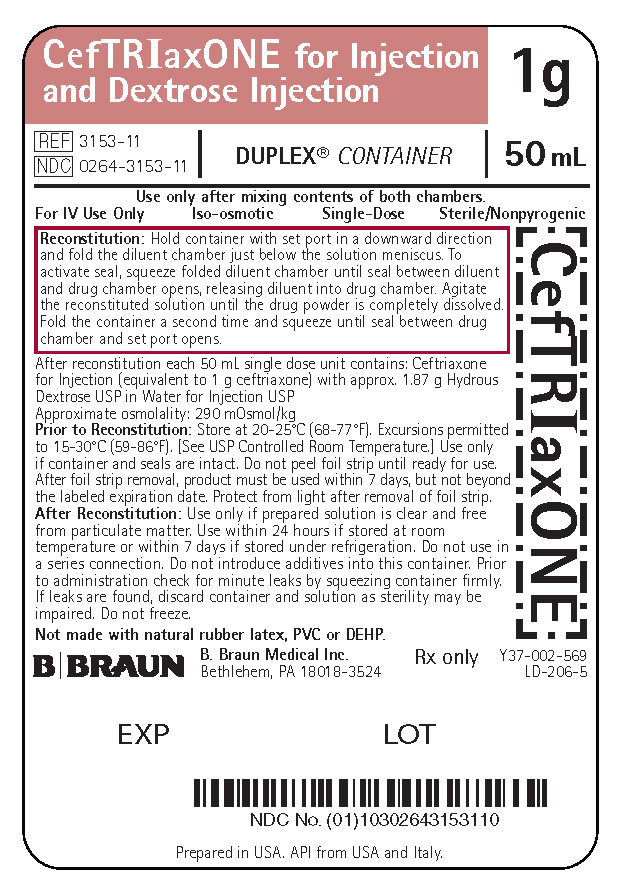 DRUG LABEL: CEFTRIAXONE AND DEXTROSE
NDC: 0264-3153 | Form: INJECTION, SOLUTION
Manufacturer: B. Braun Medical Inc.
Category: prescription | Type: HUMAN PRESCRIPTION DRUG LABEL
Date: 20220113

ACTIVE INGREDIENTS: CEFTRIAXONE SODIUM 1 g/50 mL
INACTIVE INGREDIENTS: DEXTROSE MONOHYDRATE 1.87 g/50 mL; WATER

HIGHLIGHTS OF PRESCRIBING INFORMATION

These highlights do not include all the information needed to use CEFTRIAXONE for injection and DEXTROSE injection safely and effectively. See full prescribing information for CEFTRIAXONE for injection and DEXTROSE injection.
CEFTRIAXONE for injection and DEXTROSE injection, for intravenous use
Initial U.S. Approval: 2005

RECENT MAJOR CHANGES

Warnings and Precautions, Neurological Adverse Reactions (5.3) 1/2022

1 INDICATIONS AND USAGE

Ceftriaxone for Injection and Dextrose Injection is a cephalosporin antibacterial indicated for the treatment of the following infections caused by susceptible isolates of the designated bacteria: Lower Respiratory Tract Infections (1.1); Skin and Skin Structure Infections (1.2); Complicated and Uncomplicated Urinary Tract Infections (1.3); Pelvic Inflammatory Disease (1.4); Bacterial Septicemia (1.5); Bone and Joint Infections (1.6); Intra-abdominal Infections (1.7); Meningitis (1.8); and Surgical Prophylaxis (1.9).

To reduce the development of drug-resistant bacteria and maintain the effectiveness of Ceftriaxone for Injection and Dextrose Injection and other antibacterial drugs, Ceftriaxone for Injection and Dextrose Injection should be used only to treat or prevent infections that are proven or strongly suspected to be caused by bacteria. (1.10)

2 DOSAGE AND ADMINISTRATION

For intravenous use only over approximately 30 minutes. (2)

Use this formulation of ceftriaxone only in patients who require the entire 1 or 2 gram dose and not any fraction thereof. (2.1)

Recommended Dosing Schedule for Ceftriaxone for Injection and Dextrose Injection
Site and Type of Infection | Dose | Frequency | Total Daily Dose
Usual Adult Dose | 1 g to 2 g | once a day or in equally divided doses every 12 hours | should not exceed 4 g [Patients with hepatic impairment and significant renal impairment should not receive more than 2 grams per day of ceftriaxone.]
Surgical Prophylaxis | 1 gram IV; once | 1/2 to 2 hours before surgery
Meningitis | 100 mg/kg | once a day or in equally divided doses every 12 hours | should not exceed 4 g
Skin and Skin Structure Infections | 50 mg/kg to 75 mg/kg | once a day or in equally divided doses every 12 hours | should not exceed 2 g
Serious Infections other than Meningitis | 50 mg/kg to 75 mg/kg | every 12 hours | should not exceed 2 g

3 DOSAGE FORMS AND STRENGTHS

DUPLEX® CONTAINER dual chamber, single-dose container consisting of:

- 1 g ceftriaxone for injection and 50 mL of 3.74% dextrose injection (3)
- 2 g ceftriaxone for injection and 50 mL of 2.22% dextrose injection (3)

4 CONTRAINDICATIONS

- Anaphylaxis to ceftriaxone or other cephalosporin class antibacterials, penicillins, or other beta-lactam antibacterials (4.1)

5 WARNINGS AND PRECAUTIONS

- Hypersensitivity reactions: Include anaphylaxis and serious skin reactions. Cross-hypersensitivity may occur in up to 10% of patients with a history of penicillin allergy. If an allergic reaction occurs, discontinue the drug. (5.1)
- Interaction with Calcium-containing Products: Precipitation can occur. Do not administer simultaneously with calcium-containing IV solutions. (5.2)
- Clostridioides difficile-associated diarrhea: May range from mild diarrhea to fatal colitis. Evaluate if diarrhea occurs. (5.3)
- Neurological Adverse Reactions: Serious neurological adverse reactions have been reported. If neurological adverse reactions occur, discontinue Ceftriaxone for Injection and Dextrose Injection therapy and institute appropriate supportive measures. Make appropriate dosage adjustments in patients with severe renal impairment (2.1, 5.3).
- Hemolytic Anemia: Severe cases of hemolytic anemia, including fatalities in adults and children, have been reported. If anemia is diagnosed, discontinue the drug until the etiology is determined. (5.4)

6 ADVERSE REACTIONS

The most common adverse reactions occurring in greater than 2% of patients receiving ceftriaxone include diarrhea, eosinophilia, thrombocytosis, leukopenia, and elevations of SGOT and SGPT.

To report SUSPECTED ADVERSE REACTIONS, contact B. Braun Medical Inc. at 1-800-854-6851 or FDA at 1-800-FDA-1088 or www.fda.gov/medwatch.

7 DRUG INTERACTIONS

- Vancomycin, amsacrine, aminoglycosides, and fluconazole are physically incompatible. (7.1)
- Calcium-containing products: precipitation can occur. (7.2)

8 USE IN SPECIFIC POPULATIONS

Hepatic and renal impairment

- Patients with both hepatic and renal impairment should not receive more than 2 grams of ceftriaxone per day (5.8)

Pediatric Patients

- Ceftriaxone for Injection and Dextrose Injection in the DUPLEX® Container is designed to deliver a 1 g or 2 g dose of ceftriaxone. To prevent unintentional overdose, this product should not be used in pediatric patients who require less than the full adult dose of ceftriaxone. (2.2, 8.4)

12.4 Microbiology

To reduce the development of drug-resistant bacteria and maintain the effectiveness of Ceftriaxone for Injection and Dextrose Injection and other antibacterial drugs, Ceftriaxone for Injection and Dextrose Injection should be used only to treat or prevent infections that are proven or strongly suspected to be caused by bacteria. (1)

FULL PRESCRIBING INFORMATION

RECENT MAJOR CHANGES

Warnings and Precautions, Neurological Adverse Reactions (5.3) 10/2021

1 INDICATIONS AND USAGE

Ceftriaxone for Injection and Dextrose Injection is indicated for the treatment of the following infections when caused by susceptible bacteria.

1.1 Lower Respiratory Tract Infections

Lower respiratory tract infections caused by Streptococcus pneumoniae, Staphylococcus aureus, Haemophilus influenzae, Haemophilus parainfluenzae, Klebsiella pneumoniae, Escherichia coli, Enterobacter aerogenes, Proteus mirabilis or Serratia marcescens.

1.2 Skin and Skin Structure Infections

Skin and skin structure infections caused by Staphylococcus aureus, Staphylococcus epidermidis, Streptococcus pyogenes, Viridans group streptococci, Escherichia coli, Enterobacter cloacae, Klebsiella oxytoca, Klebsiella pneumoniae, Proteus mirabilis, Morganella morganii [The efficacy for these organisms in this organ system were studied in fewer than ten infections.] , Pseudomonas aeruginosa, Serratia marcescens, Acinetobacter calcoaceticus, Bacteroides fragilis or Peptostreptococcus species.

1.3 Complicated and Uncomplicated Urinary Tract Infections

Complicated and uncomplicated urinary tract infections caused by Escherichia coli, Proteus mirabilis, Proteus vulgaris, Morganella morganii or Klebsiella pneumoniae.

1.4 Pelvic Inflammatory Disease

Pelvic inflammatory disease caused by Neisseria gonorrhoeae. Ceftriaxone sodium, like other cephalosporins, has no activity against Chlamydia trachomatis. Therefore, when cephalosporins are used in the treatment of patients with pelvic inflammatory disease and Chlamydia trachomatis is one of the suspected pathogens, appropriate antichlamydial coverage should be added.

1.5 Bacterial Septicemia

Bacterial septicemia caused by Staphylococcus aureus, Streptococcus pneumoniae, Escherichia coli, Haemophilus influenzae or Klebsiella pneumoniae.

1.6 Bone and Joint Infections

Bone and joint infections caused by Staphylococcus aureus, Streptococcus pneumoniae, Escherichia coli, Proteus mirabilis, Klebsiella pneumoniae or Enterobacter species.

1.7 Intra-abdominal Infections

Intra-abdominal infections caused by Escherichia coli, Klebsiella pneumoniae, Bacteroides fragilis, Clostridium species or Peptostreptococcus species.

1.8 Meningitis

Meningitis caused by Haemophilus influenzae, Neisseria meningitidis or Streptococcus pneumoniae. Ceftriaxone sodium has also been used successfully in a limited number of cases of meningitis and shunt infection caused by Staphylococcus epidermidis and Escherichia coli, however, the efficacy for these organisms in this organ system were studied in fewer than ten infections.

1.9 Surgical Prophylaxis

The preoperative administration of a single 1 g dose of Ceftriaxone for Injection and Dextrose Injection may reduce the incidence of postoperative infections in patients undergoing surgical procedures classified as contaminated or potentially contaminated (e.g., vaginal or abdominal hysterectomy or cholecystectomy for chronic calculous cholecystitis in high-risk patients, such as those over 70 years of age, with acute cholecystitis not requiring therapeutic antimicrobials, obstructive jaundice or common duct bile stones) and in surgical patients for whom infection at the operative site would present serious risk (e.g., during coronary artery bypass surgery). Although ceftriaxone sodium has been shown to have been as effective as cefazolin in the prevention of infection following coronary artery bypass surgery, no placebo-controlled trials have been conducted to evaluate any cephalosporin antibacterial in the prevention of infection following coronary artery bypass surgery.

1.10 Usage

To reduce the development of drug-resistant bacteria and maintain the effectiveness of Ceftriaxone for Injection and Dextrose Injection and other antibacterial drugs, Ceftriaxone for Injection and Dextrose Injection should be used only to treat or prevent infections that are proven or strongly suspected to be caused by susceptible bacteria. When culture and susceptibility information are available, they should be considered in selecting or modifying antibacterial therapy. In the absence of such data, local epidemiology and susceptibility patterns may contribute to the empiric selection of therapy.

2 DOSAGE AND ADMINISTRATION

2.1 Adult Population

Ceftriaxone for Injection and Dextrose Injection in the DUPLEX® Container should be used only in patients who require the entire 1 or 2 gram dose and not any fraction thereof. The recommended adult dosages are outlined in Table 1. Ceftriaxone for Injection and Dextrose Injection should be administered intravenously (IV) over approximately 30 minutes.

The usual duration of therapy is 4 to 14 days; in complicated infections, longer therapy may be required. When treating infections caused by Streptococcus pyogenes, therapy should be continued for at least 10 days.

Table 1: Recommended Dosing Schedule for Ceftriaxone for Injection and Dextrose Injection
Site and Type of Infection | Dose | Frequency | Total Daily Dose
Usual Adult Dose | 1 g to 2 g | once a day or in equally divided doses every 12 hours | should not exceed 4 g [Patients with hepatic impairment and significant renal impairment should not receive more than 2 grams per day of ceftriaxone.]
Surgical Prophylaxis | 1 gram IV once | 1/2 to 2 hours before surgery
Skin and Skin Structure Infections | 50 to 75 mg per kg | once a day or in equally divided doses every 12 hours | should not exceed 2 g
Meningitis | 100 mg per kg | once a day or in equally divided doses every 12 hours | should not exceed 4 g
Serious Infections other than Meningitis | 50 to 75 mg per kg | every 12 hours | should not exceed 2 g

2.2 Pediatric Patients

Ceftriaxone for Injection and Dextrose Injection in the DUPLEX® Container is designed to deliver a 1 g or 2 g dose of ceftriaxone. To prevent unintentional overdose, this product should not be used in pediatric patients who require less than the full adult dose of ceftriaxone. [see Use in Specific Populations (8.4)]

2.3 Preparation for Use of Ceftriaxone for Injection and Dextrose Injection in DUPLEX® Container

This reconstituted solution is for intravenous use only.

Do not use plastic containers in series connections. Such use would result in air embolism due to residual air being drawn from the primary container before administration of the fluid from the secondary container is complete. If administration is controlled by a pumping device, care must be taken to discontinue pumping action before the container runs dry or air embolism may result.

Parenteral drug products should be inspected visually for particulate matter and discoloration prior to administration. Use only if solution is clear and container and seals are intact.

DUPLEX® Container Storage

- To avoid inadvertent activation, the DUPLEX® Container should remain in the folded position until activation is intended.

Patient Labeling and Drug Powder/Diluent Inspection

- Apply patient-specific label on foil side of container. Use care to avoid activation. Do not cover any portion of foil strip with patient label.
- Unlatch side tab and unfold DUPLEX® Container (see Diagram 1).

- Visually inspect diluent chamber for particulate matter.
- Use only if container and seals are intact.
- To inspect the drug powder for foreign matter or discoloration, peel foil strip from drug chamber (see Diagram 2).

- Protect from light after removal of foil strip.
  Note: If foil strip is removed, the container should be re-folded and the side tab latched until ready to activate. The product must then be used within 7 days, but not beyond the labeled expiration date.

Reconstitution (Activation)

- Do not use directly after storage by refrigeration, allow the product to equilibrate to room temperature before patient use.
- Unfold the DUPLEX® container and point the set port in a downward direction. Starting at the hanger tab end, fold the DUPLEX® Container just below the diluent meniscus trapping all air above the fold. To activate, squeeze the folded diluent chamber until the seal between the diluent and powder opens, releasing diluent into the drug powder chamber (see Diagram 3).

- Agitate the liquid-powder mixture until the drug powder is completely dissolved.
  Note: Following reconstitution (activation), product must be used within 24 hours if stored at room temperature or within 7 days if stored under refrigeration.

Administration

- Visually inspect the reconstituted solution for particulate matter.
- Point the set port in a downwards direction. Starting at the hanger tab end, fold the DUPLEX® Container just below the solution meniscus trapping all air above the fold. Squeeze the folded DUPLEX® Container until the seal between reconstituted drug solution and set port opens, releasing liquid to set port (see Diagram 4).

- Prior to attaching the IV set, check for minute leaks by squeezing container firmly. If leaks are found, discard container and solution as sterility may be compromised.
- Using aseptic technique, peel foil cover from the set port and attach sterile administration set (see Diagram 5).

- Refer to directions for use accompanying the administration set.

Important Administration Instructions

- Do not use in series connections.
- Do not introduce additives into the DUPLEX® Container.
- Administer Ceftriaxone for Injection and Dextrose Injection intravenously over approximately 30 minutes.
- After the indicated stability time periods, unused portions of solutions should be discarded.
- Vancomycin, amsacrine, aminoglycosides, and fluconazole are physically incompatible with ceftriaxone in admixtures. When any of these drugs are to be administered concomitantly with ceftriaxone by intermittent intravenous infusion, it is recommended that they be given sequentially, with thorough flushing of the intravenous lines (with 0.9% sodium chloride injection or 5% dextrose in water (D5W)) between the administrations.
- Ceftriaxone for Injection and Dextrose Injection should not be physically mixed with or piggybacked into solutions containing other antimicrobial drugs due to possible incompatibility. [see Drug Interactions (7.1)]
- Precipitation of ceftriaxone-calcium can also occur when Ceftriaxone for Injection and Dextrose Injection is mixed with calcium-containing solutions in the same IV administration line. Ceftriaxone for Injection and Dextrose Injection must not be administered simultaneously with calcium-containing IV solutions, including continuous calcium-containing infusions such as parenteral nutrition via a Y-site. However, in patients other than neonates, Ceftriaxone for Injection and Dextrose Injection and calcium-containing solutions may be administered sequentially of one another if the infusion lines are thoroughly flushed between infusions with a compatible fluid. [see Warnings and Precautions (5.2)]
- There have been no reports of an interaction between ceftriaxone and oral calcium-containing products or interaction between intramuscular ceftriaxone and calcium-containing products (IV or oral).

3 DOSAGE FORMS AND STRENGTHS

Dual-chamber, single-dose container:

- 1 g ceftriaxone for injection and 50 mL of 3.74% dextrose injection
- 2 g ceftriaxone for injection and 50 mL of 2.22% dextrose injection

4 CONTRAINDICATIONS

4.1 Anaphylaxis to Ceftriaxone or the Cephalosporin Class of Antibacterials, Penicillins, or Other Beta-lactam Antibacterials

Ceftriaxone for Injection and Dextrose Injection is contraindicated in patients who have a history of anaphylaxis to ceftriaxone or the cephalosporin class of antibacterials, penicillins, or other beta-lactam antibacterials [see Warnings and Precautions (5.1)].

5 WARNINGS AND PRECAUTIONS

5.1 Hypersensitivity Reactions to Ceftriaxone, Cephalosporins, Penicillins, or Other Drugs

Serious, occasionally fatal, hypersensitivity (anaphylactic) reactions have been reported with ceftriaxone. Before therapy with Ceftriaxone for Injection and Dextrose Injection is instituted, careful inquiry should be made to determine whether the patient has had previous immediate hypersensitivity reactions to ceftriaxone, cephalosporins, penicillins, or other drugs. Exercise caution if this product is to be given to penicillin-sensitive patients because cross-hypersensitivity among beta-lactam antibacterials has been clearly documented and may occur in up to 10% of patients with a history of penicillin allergy. If an allergic reaction to Ceftriaxone for Injection and Dextrose Injection occurs, discontinue the drug. Serious acute hypersensitivity reactions may require treatment with epinephrine and other emergency measures including oxygen, corticosteroids, intravenous fluids, intravenous antihistamines, pressor amines, and airway management, as clinically indicated.

5.2 Interaction with Calcium-containing Products

Precipitation of ceftriaxone-calcium can occur when Ceftriaxone for Injection and Dextrose Injection is mixed with calcium-containing solutions in the same IV administration line. Ceftriaxone for Injection and Dextrose Injection must not be administered simultaneously with calcium-containing IV solutions, including continuous calcium-containing infusions such as parenteral nutrition via a Y-site. However, in patients other than neonates, Ceftriaxone for Injection and Dextrose Injection and calcium-containing solutions may be administered sequentially of one another if the infusion lines are thoroughly flushed between infusions with 0.9% sodium chloride injection or D5W. In vitro studies using adult and neonatal plasma from umbilical cord blood demonstrated that neonates have an increased risk of precipitation of ceftriaxone-calcium. [see Drug Interactions (7.2)]

5.3 Neurological Adverse Reactions

Serious neurological adverse reactions have been reported during postmarketing surveillance with ceftriaxone use. These reactions include encephalopathy (disturbance of consciousness including somnolence, lethargy, and confusion), seizures, myoclonus, and non-convulsive status epilepticus [see Adverse Reactions (6.2)]. Some cases occurred in patients with severe renal impairment who did not receive appropriate dosage adjustment. However, in other cases, neurological adverse reactions occurred in patients receiving an appropriate dosage adjustment. The neurological adverse reactions were reversible and resolved after discontinuation. If neurological adverse reactions associated with Ceftriaxone for Injection and Dextrose Injection therapy occur, discontinue Ceftriaxone for Injection and Dextrose Injection and institute appropriate supportive measures. Make appropriate dosage adjustments in patients with severe renal impairment [see Dosage and Administration (2.1)].

5.4 Clostridioides difficile-associated Diarrhea

Clostridioides difficile-associated diarrhea (CDAD) has been reported with use of nearly all antibacterial agents, including ceftriaxone, and may range in severity from mild diarrhea to fatal colitis. Treatment with antibacterial agents alters the normal flora of the colon leading to overgrowth of C. difficile.

C. difficile produces toxins A and B, which contribute to the development of CDAD. Hypertoxin-producing strains of C. difficile cause increased morbidity and mortality, as these infections can be refractory to antimicrobial therapy and may require colectomy. CDAD must be considered in all patients who present with diarrhea following antibacterial use. Careful medical history is necessary since CDAD has been reported to occur over two months after the administration of antibacterial agents.

If CDAD is suspected or confirmed, ongoing antibacterial use not directed against C. difficile may need to be discontinued. Appropriate fluid and electrolyte management, protein supplementation, antibacterial treatment of C. difficile, and surgical evaluation should be instituted as clinically indicated.

5.5 Hemolytic Anemia

An immune mediated hemolytic anemia has been observed in patients receiving cephalosporin class antibacterials including ceftriaxone. Severe cases of hemolytic anemia, including fatalities, have been reported during treatment in both adults and children. If a patient develops anemia while on Ceftriaxone for Injection and Dextrose Injection, the diagnosis of a cephalosporin associated anemia should be considered and Ceftriaxone for Injection and Dextrose Injection stopped until the etiology is determined.

5.6 Hypersensitivity to Dextrose Products

Hypersensitivity reactions, including anaphylaxis, have been reported with administration of dextrose products. These reactions have been reported in patients receiving high concentrations of dextrose (i.e. 50% dextrose)^1. The reactions have also been reported when corn-derived dextrose solutions were administered to patients with or without a history of hypersensitivity to corn products^2.

5.7 Gallbladder Pseudolithiasis

Ceftriaxone-calcium precipitates in the gallbladder have been observed in patients receiving ceftriaxone. These precipitates appear on sonography as an echo without acoustical shadowing suggesting sludge or as an echo with acoustical shadowing which may be misinterpreted as gallstones. The probability of such precipitates appears to be greatest in pediatric patients. Patients may be asymptomatic or may develop symptoms of gallbladder disease. The condition appears to be reversible upon discontinuation of ceftriaxone and institution of conservative management. Discontinue ceftriaxone in patients who develop signs and symptoms suggestive of gallbladder disease and/or the sonographic findings described above.

5.8 Urolithiasis and Post-Renal Acute Renal Failure

Ceftriaxone-calcium precipitates in the urinary tract have been observed in patients receiving ceftriaxone and may be detected as sonographic abnormalities. The probability of such precipitates appears to be greatest in pediatric patients. Patients may be asymptomatic or may develop symptoms of urolithiasis, and ureteral obstruction and post-renal acute renal failure. The condition appears to be reversible upon discontinuation of ceftriaxone and institution of appropriate management. Ensure adequate hydration in patients receiving ceftriaxone. Discontinue ceftriaxone in patients who develop signs and symptoms suggestive of urolithiasis, oliguria or renal failure and/or the sonographic findings described above.

5.9 Patients with Hepatic and Renal Impairment

In patients with both hepatic impairment and significant renal disease, Ceftriaxone for Injection and Dextrose Injection dosage should not exceed 2 g daily.

5.10 Pancreatitis

Cases of pancreatitis, possibly secondary to biliary obstruction, have been reported in patients treated with ceftriaxone sodium. Most patients presented with risk factors for biliary stasis and biliary sludge (preceding major therapy, severe illness, total parenteral nutrition). A cofactor role of ceftriaxone-related biliary precipitation cannot be ruled out.

5.11 Development of Drug-resistant Bacteria

Prescribing Ceftriaxone for Injection and Dextrose Injection in the absence of a proven or strongly suspected bacterial infection or a prophylactic indication is unlikely to provide benefit to the patient and increases the risk of the development of drug-resistant bacteria. As with other antibacterial drugs, use of Ceftriaxone for Injection and Dextrose Injection may result in overgrowth of nonsusceptible organisms. Careful observation of the patient is essential. If superinfection occurs during therapy, appropriate measures should be taken.

5.12 Patients with Overt or Known Subclinical Diabetes Mellitus or Carbohydrate Intolerance

As with other dextrose-containing solutions, Ceftriaxone for Injection and Dextrose Injection should be prescribed with caution in patients with overt or known subclinical diabetes mellitus or carbohydrate intolerance for any reason.

5.13 Alterations in Prothrombin Time

Alterations in prothrombin times have occurred in patients treated with ceftriaxone sodium. Patients with impaired vitamin K synthesis or low vitamin K stores (e.g., chronic hepatic disease and malnutrition) may require monitoring of prothrombin time during Ceftriaxone for Injection and Dextrose Injection treatment. Vitamin K administration (10 mg weekly) may be necessary if the prothrombin time is prolonged before or during therapy.

6 ADVERSE REACTIONS

The following serious adverse reactions to ceftriaxone are described below and elsewhere in the labeling:

- Hypersensitivity reactions [see Warnings and Precautions (5.1)]
- Ceftriaxone-calcium precipitates [see Warnings and Precautions (5.2) and Drug Interactions (7.2)]
- Neurological Adverse Reactions [see Warnings and Precautions (5.3)]
- Clostridioides difficile-associated diarrhea [see Warnings and Precautions (5.4)]
- Hemolytic anemia [see Warnings and Precautions (5.5)]

6.1 Clinical Trials Experience

Because clinical trials are conducted under widely varying conditions, adverse reaction rates observed in the clinical trials of a drug cannot be directly compared to rates in the clinical trials of another drug and may not reflect the rates observed in practice. The following reactions occurred in less than or equal to 6% of the patients:

- Local reactions—pain, induration, tenderness, and phlebitis after IV administration.
- Hypersensitivity—rash, pruritus, fever or chills.
- Hematologic—eosinophilia, thrombocytosis, leucopenia, anemia, hemolytic anemia, neutropenia, lymphopenia, thrombocytopenia, and prolongation of the prothrombin time.
- Gastrointestinal—diarrhea, nausea or vomiting, and dysgeusia. The onset of pseudomembranous colitis symptoms may occur during or after antibacterial treatment [see Warnings and Precautions (5.4)].
- Hepatic—elevations of SGOT, SGPT, alkaline phosphatase, bilirubin.
- Renal—elevations of the BUN, creatinine, and the presence of casts in the urine.
- Central nervous system—headache or dizziness.
- Genitourinary—moniliasis or vaginitis.
- Miscellaneous—diaphoresis and flushing.
- Ceftriaxone-calcium precipitates—Cases of fatal reactions with ceftriaxone-calcium precipitates in lung and kidneys in neonates have been described. In some cases the infusion lines and times of administration of ceftriaxone and calcium-containing solutions differed [see Warnings and Precautions (5.2) and Drug Interactions (7.2)].
- Other observed adverse reactions—abdominal pain, agranulocytosis, allergic pneumonitis, anaphylaxis, basophilia, biliary lithiasis, bronchospasm, colitis, dyspepsia, epistaxis, flatulence, gallbladder sludge, glycosuria, hematuria, jaundice, leukocytosis, lymphocytosis, monocytosis, nephrolithiasis, palpitations, a decrease in the prothrombin time, renal precipitations, seizures, and serum sickness.

6.2 Postmarketing Experience

The following adverse reactions have been reported during postapproval use of ceftriaxone. Because these reactions are reported voluntarily from a population of uncertain size, it is not always possible to readily estimate their frequency or establish a causal relationship to drug exposure.

- Gastrointestinal—stomatitis and glossitis.
- Genitourinary—oliguria, ureteric obstruction, post-renal acute renal failure.
- Hepatic—hepatitis.
- Dermatologic—severe cutaneous adverse reactions (erythema multiforme, Stevens-Johnson syndrome or Lyell’s syndrome/toxic epidermal necrolysis), exanthema, allergic dermatitis, urticaria, and edema.
- Immunologic—Anaphylaxis (anaphylactic shock, transient leucopenia, neutropenia, agranulocytosis and thrombocytopenia).
- Neurologic – Encephalopathy, seizures, myoclonus, and non-convulsive status epilepticus [see Warnings and Precautions (5.3)].

6.3 Cephalosporin-class Adverse Reactions

In addition to the adverse reactions listed above that have been observed in patients treated with ceftriaxone, the following adverse reactions and altered laboratory tests have been reported for cephalosporin-class antibacterials:

- Adverse Reactions: Allergic reactions, drug fever, serum sickness-like reaction, renal dysfunction, toxic nephropathy, reversible hyperactivity, hypertonia, hepatic dysfunction including hepatitis, cholestasis, aplastic anemia, hemorrhage, and superinfection.
- Altered Laboratory Tests: Positive direct Coombs’ test, false-positive test for urinary glucose, and elevated lactic acid dehydrogenase (LDH).

7 DRUG INTERACTIONS

7.1 Vancomycin, Amsacrine, Aminoglycosides, and Fluconazole

Vancomycin, amsacrine, aminoglycosides, and fluconazole are physically incompatible with ceftriaxone in admixtures [see Dosage and Administration (2.3)].

7.2 Calcium-containing Products

Precipitation of ceftriaxone-calcium can occur when Ceftriaxone for Injection and Dextrose Injection is mixed with calcium-containing solutions in the same IV administration line. Ceftriaxone for Injection and Dextrose Injection must not be administered simultaneously with calcium-containing IV solutions. Ceftriaxone for Injection and Dextrose Injection and calcium-containing solutions may be administered sequentially. [see Warnings and Precautions (5.2)]

8 USE IN SPECIFIC POPULATIONS

8.1 Pregnancy

Risk Summary

Available data from published prospective cohort studies, case series, and case reports over several decades with cephalosporin use, including Ceftriaxone, in pregnant women have not established a drug-associated risk of major birth defects, miscarriage, or adverse maternal or fetal outcomes. Ceftriaxone crosses the placenta.

In animal reproduction studies, no adverse developmental effects were observed when ceftriaxone was administered to pregnant rats at doses up to approximately 2.8 times the clinical dose of 2 g/day (see Data).

The estimated background risk of major birth defects and miscarriage for the indicated population is unknown. All pregnancies have a background risk of birth defect, loss, or other adverse outcomes. In the U.S. general population, the estimated background risk of major birth defects and miscarriage in clinically recognized pregnancies is 2% to 4% and 15% to 20%, respectively.

Data

Human Data

Published literature shows that ceftriaxone crosses the placenta. While available studies cannot definitively establish the absence of risk, published data from case-control studies and case reports over several decades have not identified an association with cephalosporin use during pregnancy and major birth defects, miscarriage, or other adverse maternal or fetal outcomes. Available studies have methodologic limitations, including small sample size, retrospective data collection, and inconsistent comparator groups.

Animal Data

Reproductive studies have been performed in mice, rats, and primates at intravenous doses of 625, 586, and 84 mg/kg/day, respectively, without evidence of embryotoxicity, fetotoxicity, or teratogenicity. These doses are approximately 1.5, 2.8, and 0.8 times the clinical dose of 2 g/day based on body surface area comparisons. Ceftriaxone was tested in a Segment III (pre-postnatal) study in rats at intravenous doses of up to 586 mg/kg/day (approximately 2.8 times the clinical dose of 2 g/day based on body surface area comparison). No adverse effects were noted on various reproductive parameters during gestation and lactation, including postnatal growth, functional behavior, and reproductive ability of the offspring.

8.2 Lactation

Risk Summary

Data from published literature report that ceftriaxone is present in human milk. There are no data on the effects of Ceftriaxone on the breastfed child or on milk production. The developmental and health benefits of breastfeeding should be considered along with the mother’s clinical need for Ceftriaxone for Injection and Dextrose Injection and any potential adverse effects on the breastfed child from Ceftriaxone for Injection and Dextrose Injection or from the mother’s underlying condition.

8.4 Pediatric Use

Ceftriaxone for Injection and Dextrose Injection in the DUPLEX® Container is designed to deliver a 1 g or 2 g dose of ceftriaxone. To prevent unintentional overdose, this product should not be used in pediatric patients who require less than the full 1 g or 2 g adult dose of ceftriaxone.

8.5 Geriatric Use

Of the total number of subjects in clinical studies of ceftriaxone sodium, 32% were 60 and over. No overall differences in safety or effectiveness were observed between these subjects and younger subjects, and other reported clinical experience has not identified differences in responses between the elderly and younger patients, but greater sensitivity of some older individuals cannot be ruled out.

Ceftriaxone is known to be substantially excreted by the kidney, and the risk of adverse reactions to this drug may be greater in patients with impaired renal function. Because elderly patients are more likely to have decreased renal function, care should be taken in dose selection, and it may be useful to monitor renal function.

The pharmacokinetics of ceftriaxone were only minimally altered in geriatric patients compared to healthy adult subjects and dosage adjustments are not necessary for geriatric patients with ceftriaxone dosages up to 2 grams per day, provided there is no severe renal and hepatic impairment. [see Clinical Pharmacology (12)]

10 OVERDOSAGE

Ceftriaxone overdosage has been reported in patients with severe renal impairment. Reactions have included neurological outcomes, including encephalopathy, seizures, myoclonus, and non-convulsive status epilepticus. In the event of overdosage, discontinue Ceftriaxone for Injection and Dextrose Injection therapy and provide general supportive treatment [see Dosage and Administration (2.1) and (Warnings and Precautions (5.3)].

In the case of overdosage, drug concentration would not be reduced by hemodialysis or peritoneal dialysis. There is no specific antidote. Treatment of overdosage should be symptomatic.

11 DESCRIPTION

Ceftriaxone for Injection and Dextrose Injection is a sterile, nonpyrogenic, single-dose, packaged combination of Ceftriaxone Sodium and Dextrose Injection (diluent) in the DUPLEX® sterile container. The DUPLEX® Container is a flexible dual chamber container.

The drug chamber is filled with ceftriaxone sodium, a sterile, semisynthetic, broad-spectrum cephalosporin antibacterial for intravenous administration. Ceftriaxone sodium is (6R,7R)-7-[2-(2-Amino-4-thiazolyl)glyoxylamido]-8-oxo-3-[[(1,2,5,6-tetrahydro-2-methyl-5,6-dioxo-as-triazin-3-yl)thio]methyl]-5-thia-1-azabicyclo[4.2.0]oct-2-ene-2-carboxylic acid, 7^2-(Z)-(O-methyloxime), disodium salt, sesquaterhydrate.

The chemical formula of ceftriaxone sodium is C18H16N8Na2O7S3•3.5H2O. It has a calculated molecular weight of 661.60 and the following structural formula:

Ceftriaxone sodium is supplied as a dry powder form equivalent to either 1 g or 2 g of ceftriaxone. Ceftriaxone sodium is a white to yellowish-orange crystalline powder which is readily soluble in water, sparingly soluble in methanol and very slightly soluble in ethanol. The pH of a 1% aqueous solution is approximately 6.7. The color of ceftriaxone sodium solutions ranges from light yellow to amber, depending on the length of storage and concentration.

Ceftriaxone sodium contains approximately 83 mg (3.6 mEq) of sodium per gram of ceftriaxone activity.

The diluent chamber contains Dextrose Injection. The concentration of Hydrous Dextrose in Water for Injection USP has been adjusted to render the reconstituted drug product iso-osmotic. Dextrose USP has been added to adjust osmolality (approximately 1.87 g and 1.11 g to 1 g and 2 g dosages, respectively). Dextrose Injection is sterile, nonpyrogenic, and contains no bacteriostatic or antimicrobial agents.

Hydrous Dextrose USP has the following structural (molecular) formula:

The molecular weight of Hydrous Dextrose USP is 198.17.

After removing the peelable foil strip, activating the seals, and thoroughly mixing, the reconstituted drug product is intended for single intravenous use. When reconstituted, the approximate osmolality for the reconstituted solution for Ceftriaxone for Injection and Dextrose Injection is 290 mOsmol/kg.

Not made with natural rubber latex, PVC or DEHP.

The DUPLEX® dual chamber container is made from a specially formulated material. The product (diluent and drug) contact layer is a mixture of thermoplastic rubber and a polypropylene ethylene copolymer that contains no plasticizers. The safety of the container system is supported by USP biological evaluation procedures.

12 CLINICAL PHARMACOLOGY

12.1 Mechanism of Action

Ceftriaxone is an antibacterial drug [see Microbiology (12.4)].

12.3 Pharmacokinetics

Average plasma concentrations of ceftriaxone following a single 30-minute intravenous (IV) infusion of a 0.5, 1 or 2 g dose in healthy subjects are presented in Table 2. Multiple IV doses ranging from 0.5 to 2 g at 12- to 24-hour intervals resulted in 15% to 36% accumulation of ceftriaxone above single-dose values.

TABLE 2: Ceftriaxone Plasma Concentrations After Single-Dose Administration

Dose/Route | Average Plasma Concentrations (mcg/mL)
Dose/Route | 0.5 hr | 1 hr | 2 hr | 4 hr | 6 hr | 8 hr | 12 hr | 16 hr | 24 hr
0.5 g IV [IV doses were infused at a constant rate over 30 minutes.] | 82 | 59 | 48 | 37 | 29 | 23 | 15 | 10 | 5
1 g IV | 151 | 111 | 88 | 67 | 53 | 43 | 28 | 18 | 9
2 g IV | 257 | 192 | 154 | 117 | 89 | 74 | 46 | 31 | 15

Over a 0.15 to 3 g dose range in healthy adult subjects, the mean elimination half-life ranged from 5.8 to 8.7 hours, plasma clearance ranged from 0.58 to 1.45 L/hour, and renal clearance ranged from 0.32 to 0.73 L/hour.

Distribution

Ceftriaxone is reversibly bound to human plasma proteins and the binding of ceftriaxone decreases with increasing concentration from a value of 95% at plasma concentrations less than 25 mcg/mL to 85% at plasma concentration of 300 mcg/mL. Over a 0.15 to 3 g dose range in healthy adult subjects, the apparent volume of distribution ranged from 5.8 to 13.5 L.

Ceftriaxone crosses the blood placenta barrier.

Ceftriaxone penetrates the inflamed meninges of infants and pediatric patients. The average values of maximum plasma concentration, cerebrospinal fluid (CSF) concentrations, elimination half-life, plasma clearance and volume of distribution after a 50 mg/kg IV dose and after a 75 mg/kg IV dose in pediatric patients suffering from bacterial meningitis are shown in Table 3.

TABLE 3: Average Pharmacokinetic Parameters of Ceftriaxone in Pediatric Patients With Meningitis

 | 50 mg/kg IV | 75 mg/kg IV
Maximum Plasma Concentrations (mcg/mL) | 216 | 275
Elimination Half-life (hr) | 4.6 | 4.3
Plasma Clearance (mL/hr/kg) | 49 | 60
Volume of Distribution (mL/kg) | 338 | 373
CSF Concentration_inflamed meninges (mcg/mL) | 5.6 | 6.4
Range (mcg/mL) | 1.3 – 18.5 | 1.3 – 44
Time after dose (hr) | 3.7 (±1.6) | 3.3 (±1.4)

After a 1 g IV dose, average concentrations of ceftriaxone, determined from 1 to 3 hours after dosing, were 581 mcg/mL in the gallbladder bile, 788 mcg/mL in the common duct bile, 898 mcg/mL in the cystic duct bile, and 78.2 mcg/g in the gallbladder wall compared to a corresponding concentration of 62.1 mcg/mL in plasma.

Excretion

Ceftriaxone concentrations in urine are shown in Table 4.

TABLE 4: Urinary Concentrations of Ceftriaxone After Single-Dose Administration

Dose/Route | Average Urinary Concentrations (mcg/mL)
Dose/Route | 0-2 hr | 2-4 hr | 4-8 hr | 8-12 hr | 12-24 hr | 24-48 hr
0.5 g IV | 526 | 366 | 142 | 87 | 70 | 15
1 g IV | 995 | 855 | 293 | 147 | 132 | 32
2 g IV | 2692 | 1976 | 757 | 274 | 198 | 40

Thirty-three percent to 67% of a ceftriaxone dose was excreted in the urine as unchanged drug and the remainder was secreted in the bile and ultimately found in the feces as microbiologically inactive compounds.

The elimination of ceftriaxone is not altered by probenecid.

Special Populations

Average pharmacokinetic parameters of ceftriaxone in healthy subjects, elderly subjects, subjects with renal impairment, and subjects with liver disease are summarized in Table 5. Compared to healthy adult subjects, the pharmacokinetics of ceftriaxone were only minimally altered in elderly subjects and in patients with renal or hepatic impairment; therefore, dosage adjustments are not necessary for these patients with ceftriaxone dosages up to 2 g per day. Ceftriaxone was not removed to any significant extent from the plasma by hemodialysis. In 6 of 26 dialysis patients, the elimination rate of ceftriaxone was markedly reduced, suggesting that plasma concentrations of ceftriaxone should be monitored in these patients to determine if dosage adjustments are necessary. [see Dosage and Administration (2.1) and Warnings and Precautions (5.7)]

TABLE 5: Average Pharmacokinetic Parameters of Ceftriaxone in Humans

Subject Group | Elimination Half-Life (hr) | Plasma Clearance (L/hr) | Volume of Distribution (L)
Healthy Subjects [Dose ranged from 0.15 to 3 g;] | 5.8 – 8.7 | 0.58 – 1.45 | 5.8 – 13.5
Elderly Subjects (mean age, 70.5 yr) | 8.9 | 0.83 | 10.7
Patients with Renal Impairment
Hemodialysis Patients (0-5 mL/min) [Creatinine clearance.] | 14.7 | 0.65 | 13.7
Severe (5-15 mL/min) | 15.7 | 0.56 | 12.5
Moderate (16-30 mL/min) | 11.4 | 0.72 | 11.8
Mild (31-60 mL/min) | 12.4 | 0.70 | 13.3
Patients With Liver Disease | 8.8 | 1.1 | 13.6

Drug Interactions

Interaction with Calcium: Two in vitro studies, one using adult plasma and the other neonatal plasma from umbilical cord blood have been carried out to assess interaction of ceftriaxone and calcium. Ceftriaxone concentrations up to 1 mM (in excess of concentrations achieved in vivo following administration of 2 grams ceftriaxone infused over 30 minutes) were used in combination with calcium concentrations up to 12 mM (48 mg/dL). Recovery of ceftriaxone from plasma was reduced with calcium concentrations of 6 mM (24 mg/dL) or higher in adult plasma or 4 mM (16 mg/dL) or higher in neonatal plasma. This may be reflective of ceftriaxone-calcium precipitation.

12.4 Microbiology

Mechanism of Action

Ceftriaxone is a bactericidal agent that acts by inhibition of bacterial cell wall synthesis. Ceftriaxone has activity in the presence of some beta-lactamases, both penicillinases and cephalosporinases, of Gram-negative and Gram-positive bacteria.

Mechanism of Resistance

Resistance to ceftriaxone is primarily through hydrolysis by beta-lactamase, alteration of penicillin-binding proteins (PBPs), and decreased permeability.

Interaction with Other Antimicrobials
In an in vitro study antagonistic effects have been observed with the combination of chloramphenicol and ceftriaxone.

Ceftriaxone has been shown to be active against most isolates of the following bacteria, both in vitro and in clinical infections [see Indications and Usage (1)]:

- Gram-negative bacteria
  - Acinetobacter calcoaceticus
  - Enterobacter aerogenes
  - Enterobacter cloacae
  - Escherichia coli
  - Haemophilus influenzae
  - Haemophilus parainfluenzae
  - Klebsiella oxytoca
  - Klebsiella pneumoniae
  - Moraxella catarrhalis
  - Morganella morganii
  - Neisseria gonorrhoeae
  - Neisseria meningitidis
  - Proteus mirabilis
  - Proteus vulgaris
  - Pseudomonas aeruginosa
  - Serratia marcescens
- Gram-positive bacteria
  - Staphylococcus aureus
  - Staphylococcus epidermidis
  - Streptococcus pneumoniae
  - Streptococcus pyogenes
  - Viridans group streptococci
- Anaerobic bacteria
  - Bacteroides fragilis
  - Clostridium species
  - Peptostreptococcus species

The following in vitro data are available, but their clinical significance is unknown. At least 90 percent of the following microorganisms exhibit an in vitro minimum inhibitory concentration (MIC) less than or equal to the susceptible breakpoint for ceftriaxone. However, the efficacy of ceftriaxone in treating clinical infections due to these microorganisms has not been established in adequate and well-controlled clinical trials.

- Gram-negative bacteria
  - Citrobacter diversus
  - Citrobacter freundii
  - Providencia species (including Providencia rettgeri)
  - Salmonella species (including Salmonella typhi)
  - Shigella species
- Gram-positive bacteria
  - Streptococcus agalactiae
- Anaerobic bacteria
  - Porphyromonas (Bacteroides) melaninogenicus
  - Prevotella (Bacteroides) bivius

Susceptibility Testing

For specific information regarding susceptibility test interpretive criteria, and associated test methods and quality control standards recognized by FDA for this drug, please see: http://www.fda.gov/STIC.

13 NONCLINICAL TOXICOLOGY

13.1 Carcinogenesis, Mutagenesis, Impairment of Fertility

Carcinogenesis

Considering the maximum duration of treatment and the class of the compound, carcinogenicity studies with ceftriaxone in animals have not been performed. The maximum duration of animal toxicity studies was 6 months.

Mutagenesis

Genetic toxicology tests included the Ames test, a micronucleus test and a test for chromosomal aberrations in human lymphocytes cultured in vitro with ceftriaxone. Ceftriaxone showed no potential for genotoxic activity in these studies.

Impairment of Fertility

Ceftriaxone produced no impairment of fertility when given intravenously to rats at daily doses up to 586 mg/kg/day, approximately 2.8 times (mg/m^2 comparison) the recommended clinical dose of 2 g/day.

13.2 Animal Toxicology and/or Animal Pharmacology

Concretions consisting of the precipitated calcium salt of ceftriaxone have been found in the gallbladder bile of dogs and baboons treated with ceftriaxone.

These appeared as a gritty sediment in dogs that received 100 mg/kg/day for 4 weeks.

A similar phenomenon has been observed in baboons but only after a protracted dosing period (6 months) at higher dose levels (335 mg/kg/day or more).

15 REFERENCES

1. Czarny D, Prichard PJ, Fennessy M, Lewis S. Anaphylactoid reaction to 50% solution of dextrose. Med J Aust 1980;2:255-258.
2. Guharoy, SR, Barajas M. Probably Anaphylactic Reaction to Corn-Derived Dextrose Solution. Vet Hum Toxicol 1991;33:609-610.

16 HOW SUPPLIED/STORAGE AND HANDLING

Ceftriaxone for Injection and Dextrose Injection in the DUPLEX® Container is a flexible dual chamber container supplied in two concentrations. After reconstitution, the concentrations are equivalent to 1 g and 2 g ceftriaxone. The diluent chamber contains approximately 50 mL of Dextrose Injection. Dextrose Injection has been adjusted to 3.74% and 2.22% for the 1 g and 2 g doses, respectively, such that the reconstituted solution is iso-osmotic.

Ceftriaxone for Injection and Dextrose Injection is supplied sterile and nonpyrogenic in the DUPLEX® Container packaged 24 single-dose units per case.

NDC | REF | Dose | Volume
0264-3153-11 | 3153-11 | 1 g | 50 mL
0264-3155-11 | 3155-11 | 2 g | 50 mL

Store the unactivated unit at 20-25°C (68-77°F). Excursions permitted to 15-30°C (59-86°F). [See USP Controlled Room Temperature.] Do not freeze.

Precautions

As with other cephalosporins, reconstituted Ceftriaxone for Injection and Dextrose Injection tends to darken depending on storage conditions, within the stated recommendations. However, product potency is not adversely affected.

Use only if prepared solution is clear and free from particulate matter.

Do not use in series connection.

Do not introduce additives into the DUPLEX® container.

17 PATIENT COUNSELING INFORMATION

Serious Allergic Reactions

Patients should be advised that allergic reactions, including serious allergic reactions could occur and that serious reactions require immediate treatment and discontinuation of ceftriaxone. Patients should report to their health care provider any previous allergic reactions to ceftriaxone, cephalosporins, penicillins, or other similar antibacterials.

Neurological Adverse Reactions

Advise patients that neurological adverse reactions could occur with Ceftriaxone for Injection and Dextrose Injection use. Instruct patients or their caregivers to inform their healthcare provider at once of any neurological signs and symptoms, including encephalopathy (disturbance of consciousness including somnolence, lethargy, and confusion), seizures, myoclonus, and non-convulsive status epilepticus, for immediate treatment, or discontinuation of Ceftriaxone for Injection and Dextrose Injection [see Warnings and Precautions (5.3)].

Diarrhea

Patients should be advised that diarrhea is a common problem caused by antibacterials, which usually ends when the antibacterial is discontinued. Sometimes after starting treatment with antibacterials, patients can develop watery and bloody stools (with or without stomach cramps and fever) even as late as two or more months after having taken the last dose of the antibacterial. If this occurs, patients should contact a physician as soon as possible.

Antibacterial Resistance

Patients should be counseled that antibacterial drugs, including Ceftriaxone for Injection and Dextrose Injection should only be used to treat bacterial infections. They do not treat viral infections (e.g., the common cold). When Ceftriaxone for Injection and Dextrose Injection is prescribed to treat a bacterial infection, patients should be told that although it is common to feel better early in the course of therapy, the medication should be taken exactly as directed. Skipping doses or not completing the full course of therapy may (1) decrease the effectiveness of the immediate treatment and (2) increase the likelihood that bacteria will develop resistance and will not be treatable by Ceftriaxone for Injection and Dextrose Injection or other antibacterial drugs in the future.

DUPLEX is a registered trademark of B. Braun Medical Inc.
ATCC is a registered trademark of the American Type Culture Collection.

B. Braun Medical Inc.
Bethlehem, PA 18018-3524 USA
1-800-227-2862
Prepared in USA. API from USA and Italy.

Y36-003-050 LD-104-7

PACKAGE LABEL

PRINCIPAL DISPLAY PANEL

CefTRIaxONE for Injection
and Dextrose Injection

1g

REF 3153-11
NDC 0264-3153-11

DUPLEX® CONTAINER

50 mL

Use only after mixing contents of both chambers.
For IV Use Only Iso-osmotic Single-Dose Sterile/Nonpyrogenic

Reconstitution: Hold container with set port in a downward direction and fold the diluent chamber just below the solution meniscus. To activate seal, squeeze folded diluent chamber until seal between diluent and drug chamber opens, releasing diluent into drug chamber. Agitate the reconstituted solution until the drug powder is completely dissolved. Fold the container a second time and squeeze until seal between drug chamber and set port opens.

After reconstitution each 50 mL single dose unit contains: Ceftriaxone for Injection (equivalent to 1 g ceftriaxone) with approx. 1.87 g Hydrous Dextrose USP in Water for Injection USP
Approximate osmolality: 290 mOsmol/kg

Prior to Reconstitution: Store at 20-25°C (68-77°F). Excursions permitted to 15-30°C (59-86°F). [See USP Controlled Room Temperature.] Use only if container and seals are intact. Do not peel foil strip until ready for use. After foil strip removal, product must be used within 7 days, but not beyond the labeled expiration date. Protect from light after removal of foil strip.

After Reconstitution: Use only if prepared solution is clear and free from particulate matter. Use within 24 hours if stored at room temperature or within 7 days if stored under refrigeration. Do not use in a series connection. Do not introduce additives into this container. Prior to administration check for minute leaks by squeezing container firmly. If leaks are found, discard container and solution as sterility may be impaired. Do not freeze.

Not made with natural rubber latex, PVC or DEHP.

B. Braun Medical Inc.
Bethlehem, PA 18018-3524

Rx only

Prepared in USA. API from USA and Italy.

Y37-002-569
LD-206-5

EXP
LOT

PEEL HERE

Drug Chamber

Discard unit if foil strip is damaged. Peel foil strip only when ready for use. Visually inspect drug prior to reconstitution.
See package insert for complete directions for reconstitution and administration.

LD-336-1 X27-001-485

PACKAGE LABEL

PRINCIPAL DISPLAY PANEL

CefTRIaxONE for Injection
and Dextrose Injection

2g

REF 3155-11
NDC 0264-3155-11

DUPLEX® CONTAINER

50 mL

Use only after mixing contents of both chambers.
For IV Use Only Iso-osmotic Single-Dose Sterile/Nonpyrogenic

Reconstitution: Hold container with set port in a downward direction and fold the diluent chamber just below the solution meniscus. To activate seal, squeeze folded diluent chamber until seal between diluent and drug chamber opens, releasing diluent into drug chamber. Agitate the reconstituted solution until the drug powder is completely dissolved. Fold the container a second time and squeeze until seal between drug chamber and set port opens.

After reconstitution each 50 mL single dose unit contains: Ceftriaxone for Injection (equivalent to 2 g ceftriaxone) with approx. 1.11 g Hydrous Dextrose USP in Water for Injection USP
Approximate osmolality: 290 mOsmol/kg

Prior to Reconstitution: Store at 20-25°C (68-77°F). Excursions permitted to 15-30°C (59-86°F). [See USP Controlled Room Temperature.] Use only if container and seals are intact. Do not peel foil strip until ready for use. After foil strip removal, product must be used within 7 days, but not beyond the labeled expiration date. Protect from light after removal of foil strip.

After Reconstitution: Use only if prepared solution is clear and free from particulate matter. Use within 24 hours if stored at room temperature or within 7 days if stored under refrigeration. Do not use in a series connection. Do not introduce additives into this container. Prior to administration check for minute leaks by squeezing container firmly. If leaks are found, discard container and solution as sterility may be impaired. Do not freeze.

Not made with natural rubber latex, PVC or DEHP.

B. Braun Medical Inc.
Bethlehem, PA 18018-3524

Rx only

Prepared in USA. API from USA and Italy.

Y37-002-570
LD-207-5

EXP
LOT

PEEL HERE

Drug Chamber

Discard unit if foil strip is damaged. Peel foil strip only when ready for use. Visually inspect drug prior to reconstitution.
See package insert for complete directions for reconstitution and administration.

LD-336-1 X27-001-485